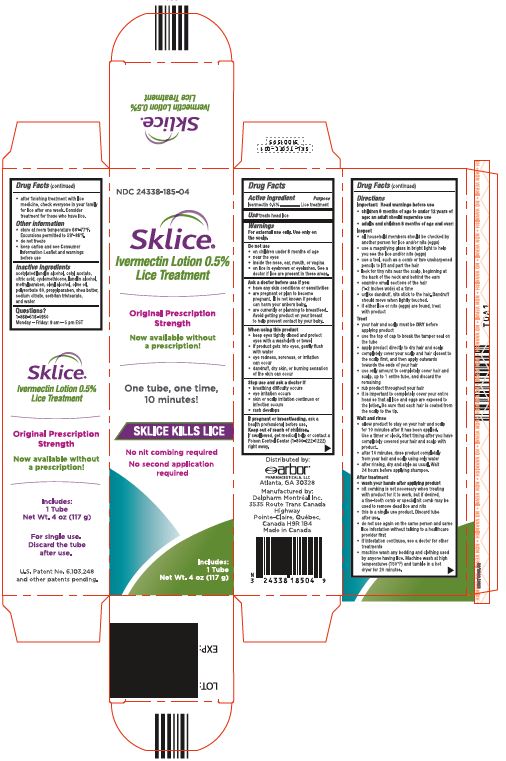 DRUG LABEL: Sklice
NDC: 24338-185 | Form: LOTION
Manufacturer: Azurity Pharmaceuticals
Category: otc | Type: HUMAN OTC DRUG LABEL
Date: 20240711

ACTIVE INGREDIENTS: IVERMECTIN 5 mg/1 g
INACTIVE INGREDIENTS: WATER; OLIVE OIL; OLEYL ALCOHOL; POLYSORBATE 80; CETYL ACETATE; LANOLIN ALCOHOLS; CYCLOMETHICONE; SHEA BUTTER; SODIUM CITRATE, UNSPECIFIED FORM; SORBITAN TRISTEARATE; METHYLPARABEN; PROPYLPARABEN; CITRIC ACID MONOHYDRATE

Sklice®

Drug Facts

Active ingredient

Ivermectin 0.5%

Purpose

Lice treatment

Use

treats head lice

Warnings

For external use only. Use only on the scalp.

Do not use

- on children under 6 months of age
- near the eyes
- inside the nose, ear, mouth, or vagina
- on lice in eyebrows or eyelashes. See a doctor if lice are present in these areas.

Ask a doctor before use if you

- have any skin conditions or sensitivities
- are pregnant or plan to become pregnant. It is not known if product can harm your unborn baby.
- are currently or planning to breastfeed. Avoid getting product on your breast to help prevent contact by your baby.

When using this product

- keep eyes tightly closed and protect eyes with a washcloth or towel
- if product gets into eyes, gently flush with water
- eye redness, soreness, or irritation can occur
- dandruff, dry skin, or burning sensation of the skin can occur

Stop use and ask a doctor if

- breathing difficulty occurs
- eye irritation occurs
- skin or scalp irritation continues or infection occurs
- rash develops

PREGNANCY OR BREAST FEEDING

If pregnant or breastfeeding,ask a health professional before use.

Keep out of reach of children.

If swallowed, get medical help or contact a Poison Control Center (1-800-222-1222) right away.

Directions

Important: Read warnings before use

- children 6 months of age to under 12 years of age: an adult should supervise use
- adults and children 6 months of age and over:

Inspect

- all household members should be checked by another person for lice and/or nits (eggs)
- use a magnifying glass in bright light to help you see the lice and/or nits (eggs)
- use a tool, such as a comb or two unsharpened pencils to lift and part the hair
- look for tiny nits near the scalp, beginning at the back of the neck and behind the ears
- examine small sections of the hair (1-2 inches wide) at a time
- unlike dandruff, nits stick to the hair. Dandruff should move when lightly touched.
- if either lice or nits (eggs) are found, treat with product

Treat

- your hair and scalp must be DRYbefore applying product
- use the top of cap to break the tamper seal on the tube
- apply product directly to dry hair and scalp
- completely cover your scalp and hair closest to the scalp first, and then apply outwards towards the ends of your hair
- use only amount to completely cover hair and scalp, up to 1 entire tube, and discard the remaining
- rub product throughout your hair
- it is important to completely cover your entire head so that all lice and eggs are exposed to the lotion. Be sure that each hair is coated from the scalp to the tip.

Wait and rinse

- allow product to stay on your hair and scalp for 10 minutes after it has been applied. Use a timer or clock. Start timing after you have completely covered your hair and scalp with product.
- after 10 minutes, rinse product completely from your hair and scalp using only water
- after rinsing, dry and style as usual. Wait 24 hours before applying shampoo.

After treatment

- wash your hands after applying product
- nit combing is not necessary when treating with product for it to work, but if desired, a fine-tooth comb or special nit comb may be used to remove dead lice and nits
- this is a single use product. Discard tube after use.
- do not use again on the same person and same lice infestation without talking to a healthcare provider first
- if infestation continues, see a doctor for other treatments
- machine wash any bedding and clothing used by anyone having lice. Machine wash at high temperatures (150°F) and tumble in a hot dryer for 20 minutes.
- after finishing treatment with lice medicine, check everyone in your family for lice after one week. Consider treatment for those who have lice.

Other information

- store at room temperature 68°-77°F. Excursions permitted to 59°-86°F.
- do not freeze
- keep carton and see Consumer Information Leaflet and warnings before use

Inactive ingredients

acetylated lanolin alcohol, cetyl acetate, citric acid, cyclomethicone, lanolin alcohol, methylparaben, oleyl alcohol, olive oil, polysorbate 80, propylparaben, shea butter, sodium citrate, sorbitan tristearate, and water

Questions?

1-866-516-4950
Monday – Friday: 9 am – 5 pm EST

Distributed by:
arbor®
PHARMACEUTICALS, LLC
Atlanta, GA 30328

Manufactured by:
Delpharm Montréal Inc.
3535 Route Trans Canada Highway
Pointe-Claire, Québec,
Canada H9R 1B4
Made in Canada

PRINCIPAL DISPLAY PANEL - 117 g Tube Carton

NDC 24338-185-04

Sklice®

Ivermectin Lotion 0.5%

Lice Treatment

Original Prescription
Strength

Now available without
a prescription!

One tube, one time,
10 minutes!

SKLICE KILLS LICE

No nit combing required

No second application
required

Includes:
1 Tube
Net Wt. 4 oz (117 g)